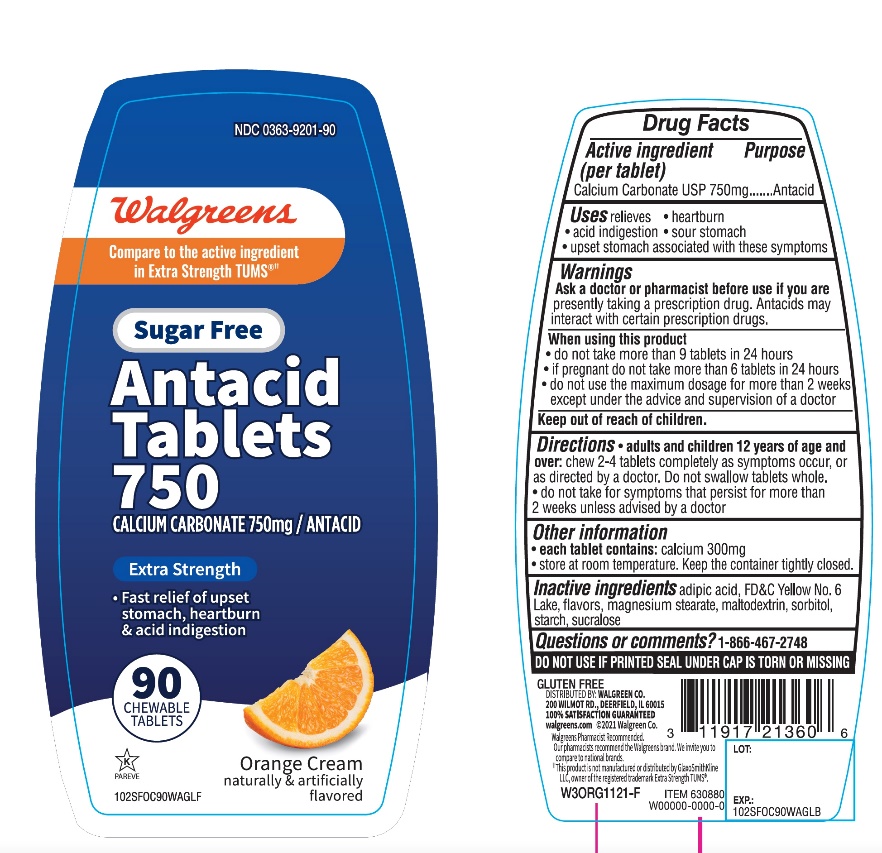 DRUG LABEL: Extra Strength Antacid
NDC: 0363-9201 | Form: TABLET, CHEWABLE
Manufacturer: WALGREEN COMPANY
Category: otc | Type: HUMAN OTC DRUG LABEL
Date: 20251125

ACTIVE INGREDIENTS: CALCIUM CARBONATE 750 mg/1 1
INACTIVE INGREDIENTS: ADIPIC ACID; FD&C YELLOW NO. 6; MAGNESIUM STEARATE; MALTODEXTRIN; SORBITOL; STARCH, CORN; SUCRALOSE

Extra Strength Antacid Tablets Calcium Carbonate 750 mg

Active ingredient (per tablet)

Calcium Carbonate USP 750 mg

Purpose

Antacid

Uses

relieves

- heartburn
- acid indigestion
- sour stomach
- upset stomach associated with these symptoms

Warnings

Ask a doctor or pharmacist before use if you arepresently taking a prescription drug. Antacids may interact with certain prescription drugs.

When using this product

- do not take more than 9 tablets in 24 hours
- if pregnant do not take more than 6 tablets in 24 hours
- do not use the maximum dosage for more than 2 weeks except under the advice and supervision of a doctor

Directions

- adults and children 12 years of age and over:chew 2-4 tablets as symptoms occur, or as directed by a doctor. Do not swallow tablets whole.
- do not take for symptoms that persist for more than 2 weeks unless advised by a doctor

Other Information

- each tablet contains:calcium 300 mg
- store at room temperature. Keep the container tightly closed

Inactive ingredients

adipic acid, FD&C Yellow No. 6 Lake, flavors, magnesium stearate, maltodextrin, sorbitol, starch, sucralose.

Questions or comments?

1-866-467-2748

DO NOT USE IF PRINTED SEAL UNDER CAP IS TORN OR MISSING

Package/Label Principal Display Panel

NDC 0363-9201-90

*Compare to the active ingredient in Extra Strength Tums®

EXTRA STRENGTH

Antacid Tablets

SUGAR FREE

Calcium Carbonate USP 750 mg

- Fast Relief of Upset
- Stomach, Heartburn
- and Acid Indigestion
- ORANGE CREAM
- NATURALLY & ARTIFICIALLY FLAVORED
- GLUTEN FREE

90 TABLETS

K PARVE

GLUTEN-FREE

DISTRIBUTED BY:

WALGREEN CO.

200 WILDMOT RD., DEERFIELD, IL 60015

100% SATISFACTION GUARANTEED

walgreens.com ©2019 Walgreen Co.

Walgreens Pharmacist Recommended

Walgreens Pharmacist Survey

††This product is not manufactured or distributed by GlaxoSmithKline LLC, owner of the registered trademark, Extra Strength TUMS®.